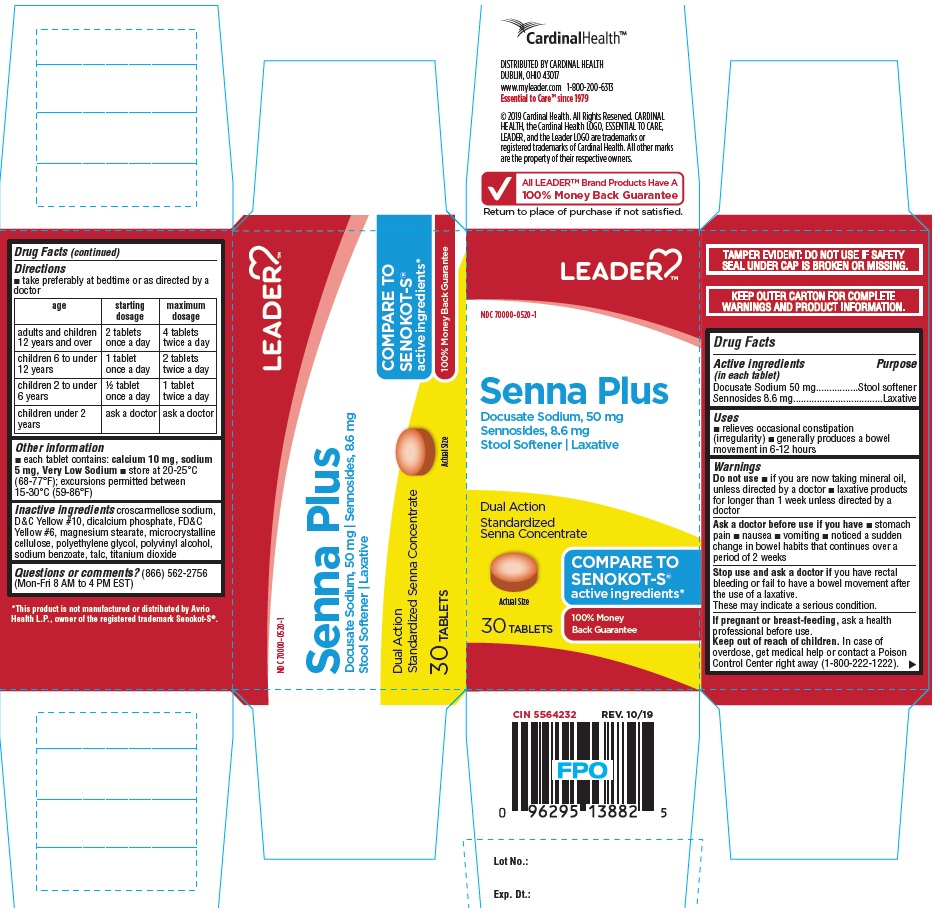 DRUG LABEL: Senna Plus
NDC: 70000-0520 | Form: TABLET, FILM COATED
Manufacturer: CARDINAL HEALTH, 110 DBA LEADER
Category: otc | Type: HUMAN OTC DRUG LABEL
Date: 20251223

ACTIVE INGREDIENTS: SENNOSIDES 8.6 mg/1 1; DOCUSATE SODIUM 50 mg/1 1
INACTIVE INGREDIENTS: CROSCARMELLOSE SODIUM; D&C YELLOW NO. 10; CALCIUM PHOSPHATE, DIBASIC, DIHYDRATE; FD&C YELLOW NO. 6; MAGNESIUM STEARATE; CELLULOSE, MICROCRYSTALLINE; POLYETHYLENE GLYCOL, UNSPECIFIED; POLYVINYL ALCOHOL, UNSPECIFIED; SODIUM BENZOATE; TALC; TITANIUM DIOXIDE

Drug Facts

Active Ingredients (in each tablet)

Docusate Sodium 50 mg

Sennosides 8.6 mg

Purpose

Stool Softener

Laxative

Uses

- relieves occasional constipation (irregularity)
- generally produces a bowel movement in 6-12 hours

Warnings

Do not use

- if you are taking mineral oil, unless directed by a doctor
- laxative products for longer than 1 week unless directed by a doctor

Ask a doctor before use if you have

- stomach pain
- nausea
- vomiting
- noticed a sudden change in bowel habits that continues over a period of 2 weeks

Stop use and ask a doctor if

you have rectal bleeding or fail to have a bowel movement after the use of a laxative.

These may indicate a serious condition.

If pregnant or breast-feeding,

ask a health professional before use.

Keep out of reach of children.

In case of overdose, get medical help or contact a Poison Control Center right away (1-800-222-1222).

Directions

- take preferably at bedtime or as directed by a doctor

age | starting dosage | maximum dosage
adults and children 12 years and over | 2 tablets once a day | 4 tablets twice a day
children 6 to under 12 years | 1 tablet once a day | 2 tablets twice a day
children 2 to under 6 years | 1/2 tablet once a day | 1 tablet twice a day
children under 2 years | ask a doctor | ask a doctor

Other information

- each tablet contains: calcium 10 mg, sodium 5 mg, Very Low Sodium
- store at 20-25°C(68-77°F); excursions permitted between 15o-30oC (59o-86oF)

Inactive ingredients

croscarmellose sodium, D&C Yellow# 10, dicalcium phosphate, FD&C Yellow #6, magnesium stearate, microcrystalline cellulose, polyethylene glycol, polyvinyl alcohol, sodium benzoate, talc, titanium dioxide

Questions or comments?

(866) 562-2756 (Mon-Fri 8 AM to 4 PM EST)

PACKAGE LABEL

LEADER TM

NDC 70000-0520-1

Senna Plus

Docusate Sodium, 50 mg

Sennosides, 8.6 mg

Stool Softener l Laxative

Dual Action

Standardized

Senna Concentrate

COMPARE TO

SENOKOT-S®

active ingredients*

100% Money

Back Guarantee

30 TABLETS